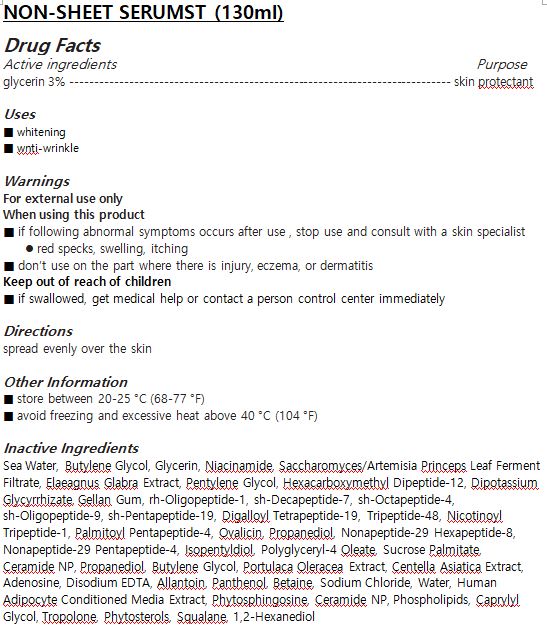 DRUG LABEL: NON-SHEET SERUMST
NDC: 72943-0003 | Form: LIQUID
Manufacturer: DAONMEDICOS CO.
Category: otc | Type: HUMAN OTC DRUG LABEL
Date: 20190324

ACTIVE INGREDIENTS: GLYCERIN 3 g/100 mL
INACTIVE INGREDIENTS: WATER; ALLANTOIN

Drug Facts

ACTIVE INGREDIENT

GLYCERIN

INACTIVE INGREDIENT

Sea Water
Water
Butylene Glycol
Glycerin
Niacinamide
Saccharomyces/Artemisia Princeps Leaf Ferment Filtrate
Elaeagnus Glabra Extract
Pentylene Glycol
Hexacarboxymethyl Dipeptide-12
Dipotassium Glycyrrhizate
Gellan Gum
rh-Oligopeptide-1
sh-Decapeptide-7
sh-Octapeptide-4
sh-Oligopeptide-9
sh-Pentapeptide-19
Digalloyl Tetrapeptide-19
Tripeptide-48
Nicotinoyl Tripeptide-1
Palmitoyl Pentapeptide-4
Ovalicin
Propanediol
Nonapeptide-29 Hexapeptide-8
Nonapeptide-29 Pentapeptide-4
Isopentyldiol
Polyglyceryl-4 Oleate
Sucrose Palmitate
Ceramide NP
Propanediol
Butylene Glycol
Portulaca Oleracea Extract
Centella Asiatica Extract
Adenosine
Disodium EDTA
Allantoin
Panthenol
Betaine
Sodium Chloride
Water
Human Adipocyte Conditioned Media Extract
Phytosphingosine
Ceramide NP
Phospholipids
Caprylyl Glycol
Tropolone
Phytosterols
Squalane
1,2-Hexanediol

PURPOSE

whitening

anti-wrinkle

keep out of reach of the children

INDICATIONS AND USAGE

spread evenly over the skin

WARNINGS

■ if following abnormal symptoms occurs after use , stop use and consult with a skin specialist

red specks, swelling, itching

■ don’t use on the part where there is injury, eczema, or dermatitis

Keep out of reach of children

■ if swallowed, get medical help or contact a person control center immediately

DOSAGE AND ADMINISTRATION

for external use only